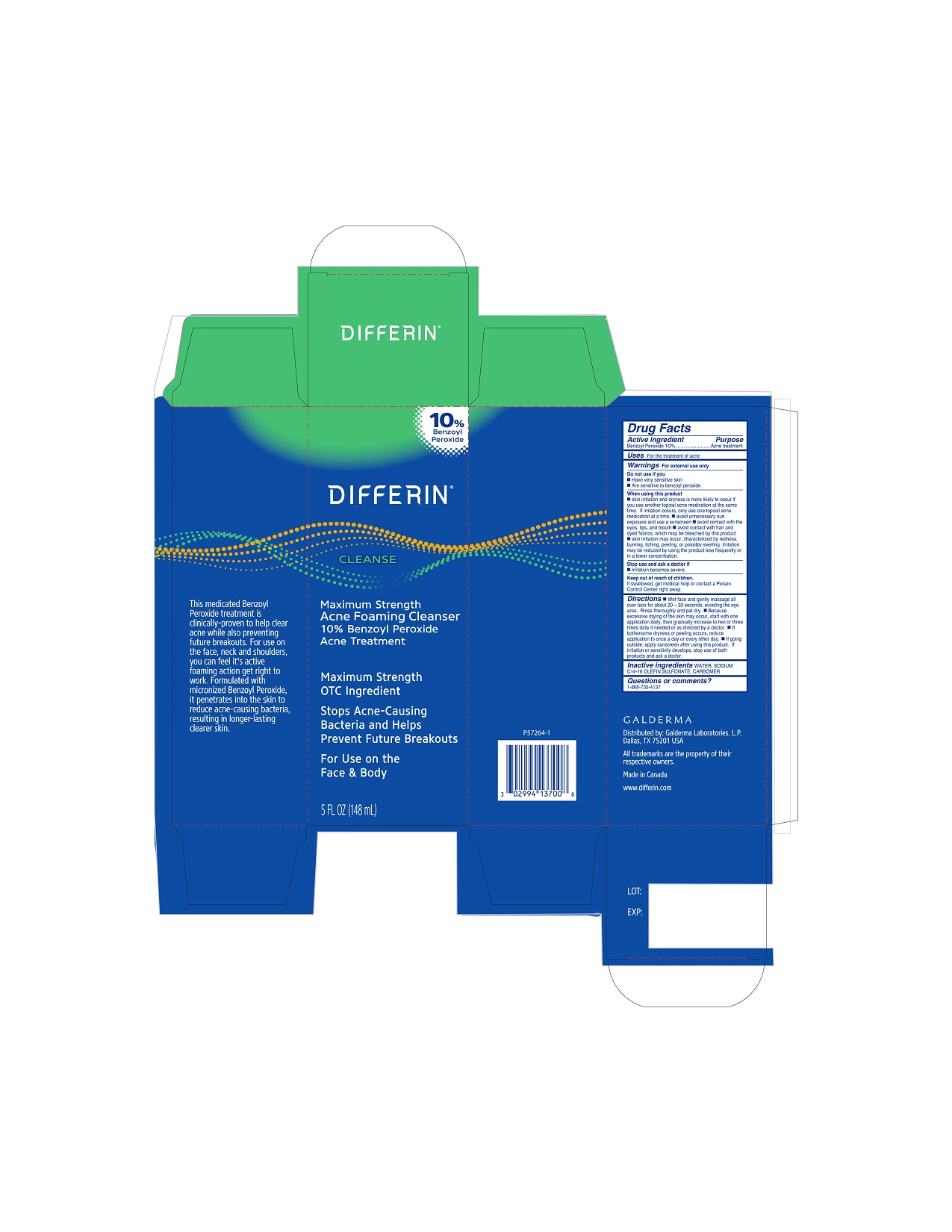 DRUG LABEL: Differin Max Strength Acne Foaming BPO Cleanser
NDC: 0299-4137 | Form: SOLUTION
Manufacturer: Galderma Laboratories, L.P.
Category: otc | Type: HUMAN OTC DRUG LABEL
Date: 20240607

ACTIVE INGREDIENTS: Benzoyl Peroxide 10 g/100 mL
INACTIVE INGREDIENTS: Water; Sodium C14-16 Olefin Sulfonate; Carbomer Homopolymer, Unspecified Type

Drug Facts

Active Ingredients

Benzoyl Peroxide 10%

Purpose

Acne treatment

Uses

For the treatment of acne

Warnings

For external use only.

Do not use if you
■ Have very sensitive skin
■ Are sensitive to benzoyl peroxide

When using this product
■ skin irritation and dryness is more likely to occur if you use another topical acne medication at the same time. If irritation occurs, only use one topical acne medication at a time. ■ avoid unnecessary sun exposure and use a sunscreen ■ avoid contact with the eyes, lips, and mouth ■ avoid contact with hair and dyed fabrics, which may be bleached by this product ■ skin irritation may occur, characterized by redness, burning, itching, peeling, or possibly swelling. Irritation may be reduced by using the product less frequently or in a lower concentration.

Stop use and ask a doctor if
■ Irritation becomes severe.

Keep out of reach of children.
If swallowed, get medical help or contact a Poison Control Center right away.

Directions

■ Wet face and gently massage all over face for about 20 – 30 seconds, avoiding the eye area. Rinse thoroughly and pat dry. ■ Because excessive drying of the skin may occur, start with one application daily, then gradually increase to two or three times daily if needed or as directed by a doctor. ■ If bothersome dryness or peeling occurs, reduce application to once a day or every other day. ■ If going outside, apply sunscreen after using this product. If irritation or sensitivity develops, stop use of both products and ask a doctor.

Inactive Ingredients

WATER, SODIUM C14-16 OLEFIN SULFONATE, CARBOMER

Questions or comments?

1-866-735-4137

QUESTIONS

Distributed by:

Galderma Laboratories, L.P.

Dallas, TX 75201
USA

All trademarks are the property of their respective owners

Made in Canada

www.differin.com

Principle Display Panel - 5 FL OZ carton

10% Benzoyl Peroxide
DIFFERIN®

CLEANSE

Maximum Strength
Acne Foaming Cleanser
10% Benzoyl Peroxide
Acne Treatment

Maximum Strength
OTC Ingredient

Stops Acne-Causing
Bacteria and Helps
Prevent Future Breakouts
For Use on the
Face & Body
5 FL OZ (148 mL)
P57264-1